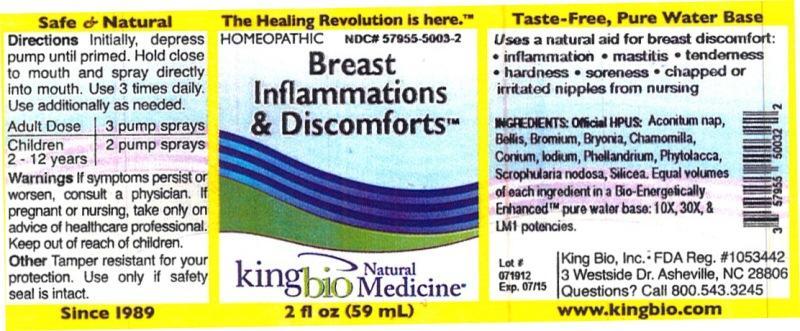 DRUG LABEL: Breast Inflammations and Discomforts
NDC: 57955-5003 | Form: LIQUID
Manufacturer: King Bio Inc.
Category: homeopathic | Type: HUMAN OTC DRUG LABEL
Date: 20121016

ACTIVE INGREDIENTS: ACONITUM NAPELLUS 10 [hp_X]/59 mL; BELLIS PERENNIS 10 [hp_X]/59 mL; BROMINE 10 [hp_X]/59 mL; BRYONIA ALBA ROOT 10 [hp_X]/59 mL; MATRICARIA RECUTITA 10 [hp_X]/59 mL; CONIUM MACULATUM FLOWERING TOP 10 [hp_X]/59 mL; IODINE 10 [hp_X]/59 mL; PHYTOLACCA AMERICANA ROOT 10 [hp_X]/59 mL; SCROPHULARIA NODOSA 10 [hp_X]/59 mL; SILICON DIOXIDE 10 [hp_X]/59 mL; OENANTHE AQUATICA FRUIT 10 [hp_X]/59 mL
INACTIVE INGREDIENTS: WATER

Breast Inflammations and Discomforts

Active Ingredients

Official HPUS: Aconitum napellus, Bellis perennis, Bromium, Bryonia, Chamomilla, Conium maculatum, Iodium, Phellandrium aquaticum, Phytolacca decandra, Scrophularia nodosa and Silicea.

Inactive Ingredient

Equal volumes of each ingredient in a Bio-Energetically Enhanced pure water base: 10X, 30X and LM1 potencies.

Purpose

Uses a natural aid for breast discomfort:

- Inflammation
- mastitis
- tenderness
- hardness
- soreness
- chapped or irritated nipples from nursing

Dosage and Administration

Directions Initially, depress pump until primed. Hold close to mouth and spray directly into mouth. Use 3 times daily. Use additionally as needed.

Adult Dose 3 pump sprays

Children 2-12 years 2 pump sprays

Warnings

If symptoms persist or worsen, consult a physician. If pregnant or nursing, take only on advice of healthcare professional. Keep out of reach of children.

Other: Tamper resistant for your protection. Use only if safety seal is intact.

Keep out of reach of children.

Indications and Usage

Uses a natural aid for breast discomfort: inflammation, mastitis, tenderness, hardness, soreness, chapped or irritated nipples from nursing.

PACKAGE LABEL

King Bio Inc.

3 Westside Drive

Asheville, NC 28806

Questions? Call 800.543.3245

www.kingbio.com